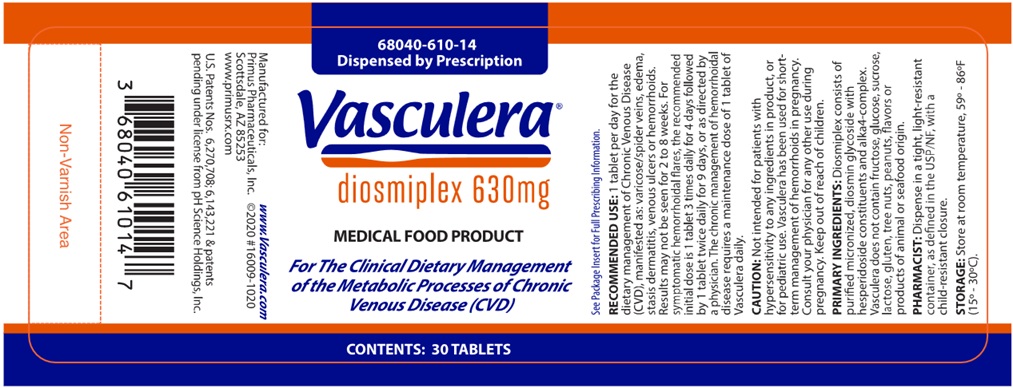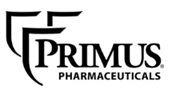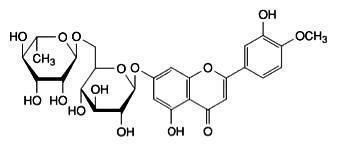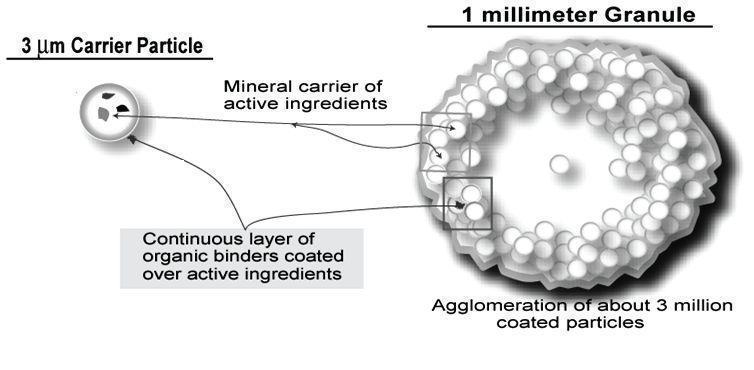 DRUG LABEL: Vasculera
NDC: 68040-610 | Form: TABLET
Manufacturer: Primus Pharmaceuticals, Inc.
Category: other | Type: MEDICAL FOOD
Date: 20250224

ACTIVE INGREDIENTS: DIOSMIN 600 mg/1 1
INACTIVE INGREDIENTS: CELLULOSE, MICROCRYSTALLINE; STEARIC ACID; CROSCARMELLOSE SODIUM; POVIDONE; SILICON DIOXIDE; WATER; OPADRY YS-1-17274A BEIGE

Product Information
VASCULERA® Tablets for oral administration.
Dispensed by prescription.
diosmiplex 630mg

VASCULERA is a specially formulated prescription medical food product for the clinical dietary management of the metabolic processes of chronic venous disease (CVD). VASCULERA must be administered under physician supervision.

DESCRIPTION

VASCULERA (diosmiplex) consists of a specially formulated proprietary blend of micronized, highly purified diosmin glycoside in combination with alkaline granules, alka4-complex. Diosmin glycoside manages venous inflammation, accumulation of polymorphonuclear leukocytes, platelets and other thrombotic components as well as edema, caused by a deterioration of venous vessel walls. Alka4-complex works by buffering stomach acid and managing blood pH to affect local metabolic acidosis in veins.

Diosmin glycoside

Each VASCULERA tablet contains 600 mg of diosmin glycoside (diosmin), a micronized, highly purified flavonoid fraction (from citrus) with hesperidoside constituents. In clinical trials, this level of intake has been shown to manage chronic venous disease (CVD). Diosmin is chemically described as (7-[[6-O-(6-Deoxy-α-L-mannopyranosyl)-ß-D-glucopyranosyl]oxy]-5-hydroxy-2-(3-hydroxy-4-methoxyphenyl)-4H-1-benzopyran-4-one) with a molecular weight of 608.5. The empirical formula for diosmin is C28H32O15. The structural formula is:

Alka4-complex

Each VASCULERA tablet contains 30 mg of a proprietary, structured, highly alkaline agglomeration of reactive magnesium hydroxide (Mg(OH)2, molecular weight 58.3), potassium chloride (KCl, molecular weight 74.6) and potassium hydroxide (KOH, molecular weight 56.1) held apart from each other in a matrix of calcium carbonate (CaCO3, molecular weight 100.1), microcrystalline cellulose and croscarmellose sodium. The agglomerated particle matrix has the following approximate characteristics:

Other Ingredients
VASCULERA contains the following other ingredients as fillers and excipients: microcrystalline cellulose, steric acid, croscarmellose sodium, povidone, silicon dioxide, tablet coating {Opadry® II (contains maltodextrin)} and water. Tablets do not contain fructose, glucose, sucrose, lactose, gluten, tree nuts, peanuts, soy, flavors or products of animal or seafood origin.
Medical Foods
The U.S. Congress defined “medical food” in the Orphan Drug Act and Amendments of 1988 as “a food which is formulated to be consumed or administered enterally under the supervision of a physician, and which is intended for the specific dietary management of a disease or condition for which distinctive nutritional requirements, based on recognized scientific principles, are established by medical evaluation.” VASCULERA has been developed, manufactured and labeled in accordance with the statutory definition of a medical food. VASCULERA is to be used only under a physician’s supervision.
Generally Recognized As Safe
The ingredients in VASCULERA are Generally Recognized as Safe (GRAS). This is the statutory U.S. safety standard that the U.S. Food and Drug Administration (FDA) requires of all ingredients added to food products. The standard for an ingredient to achieve GRAS status requires technical demonstration of non-toxicity and safety, general recognition of safety through widespread usage and agreement of that safety by experts in the field.

CHRONIC VENOUS DISEASE (CVD)

Chronic venous disease is caused by venous hypertension (VH). VH, in turn, aggravates these metabolic imbalances leading to a self-perpetuating cycle of further metabolic changes, including venous acidosis. These changes promote further inflammation in vascular tissue leading to edema, skin damage and possible ulceration and deep vein thrombosis (DVT). Varicose veins and hemorrhoids are also part of the spectrum of CVD disorders.

CLINICAL PHARMACOLOGY

Mechanism of Action

Vasculera addresses the venous inflammation associated with chronic venous disease by decreasing leukocyte activation, down regulating VEGF expression and decreasing TNF-alpha.

Diosmin glycoside

The diosmin in VASCULERA has been shown in both cell and animal models to enhance venous tone by prolonging the post-synaptic response to norepinephrine (NE) and increasing the sensitivity of vascular smooth muscle to NE and calcium, even under conditions of acidosis. Diosmin inhibits the NE degrading enzyme catechol-O-methyltransferase (COMT). Diosmin has also been shown to manage lymphatic drainage and decrease edema by increasing lymphatic vessel contraction frequency and amplitude. Venous hypertension induces production of inflammatory factors such as prostaglandins and leukotrienes, metalloproteinases, cytokines, adhesion molecules and VEGF. Localization of inflammatory cells generates high levels of tissue destructive reactive oxygen species (ROS). Diosmin acts as a scavenger of ROS, inhibits 5-lipoxygenase and the production of prostaglandins E2 and thromboxane B2, which may help to protect endothelial cells from damage associated with inflammation and acute oxidative stress.

Alka4-complex

Clinical studies have shown that alka4-complex in VASCULERA can reduce acidosis generated under extreme exercise loads. The specially agglomerated matrix of alka4-complex has been shown to resist neutralization by acid solutions. This ability to survive the acid environment of the stomach and to be taken up in the intestine may account for its effect on blood pH during exercise. Alka4-complex may counter the local acidosis produced in CVD and work synergistically with diosmin to manage venous inflammation. In addition, the alka4-complex has been shown to reduce the acid producing effects of certain foods by buffering the acidity in the gastrointestinal tract, while allowing a sufficient portion of the complex to survive in the stomach, and is absorbed in the small intestine thereby being available to manage mild acidosis.

METABOLISM

Diosmin glycoside
Diosmin is hydrolyzed to its aglycone form, diosmetin, by intestinal microorganisms and enzymes in the intestinal lumen prior to absorption. Once it reaches the liver, diosmetin is extensively glucuronidated before entering the systemic circulation. Diosmetin may also be reduced to its corresponding flavanone aglycone, hesperidin, by intestinal bacteria in second pass metabolism. No diosmin is detected in the serum in animals or humans. Only the active form diosmetin, is detected after ß-glucuronidase digestion. The phenolic acid products of diosmetin degradation are excreted in the urine, while unabsorbed/unmetabolized diosmin and diosmetin are excreted in the feces.

Alka4-complex

In contrast to sodium bicarbonate, alka4-complex has been shown in acid dissolution studies to release alkalizing salts in two gradual steps. Starting at a pH of 2, alka4-complex takes approximately 15 min to raise the solution pH to 6 whereas this occurs in seconds with bicarbonate. A further increase to a pH of 7 occurs over the next 60-90 min period. This biphasic, slow release characteristic gives alka4-complex seven times more pH neutralizing capacity compared to the same concentration of sodium bicarbonate. The molecular protection afforded by the proprietary matrix allows the alka4-complex to enter the intestinal tract where it is absorbed. Compared to bicarbonate ions, hydroxyl ions present in alka4-complex have been shown to be better absorbed by the intestinal lumen.

CLINICAL EXPERIENCE

Hepatic and Renal Effects

In multiple clinical studies, the effects of diosmin in VASCULERA on blood chemistry as well as hepatic and renal function were compared to placebo in healthy subjects and patients with CVD. No clinically significant changes were noted in hepatic or renal function.

Cardiovascular Safety

No cardio-vascular adverse effects of the diosmin in VASCULERA have been observed in clinical trials. Small decreases in both systolic and diastolic blood pressure have been noted in several studies for CVD. When used as a pretreatment for coronary artery bypass grafting, troponin I and lactate dehydrogenase levels were significantly lower in the post-cardiopulmonary bypass period.

Blood Glucose, Insulin and Insulin Resistance

No effects of diosmin or alka4-complex have been noted in clinical studies on blood glucose or insulin levels as well as insulin resistance.

DRUG INTERACTIONS

Diosmin glycoside

No evidence of drug incompatibility (drug interaction) has been reported in clinical trials or in post-marketing reports after decades of use in Europe.

TOXICITY

Diosmin glycoside

In chronic and acute toxicity studies in mice, rats and primates in single oral doses up to 3,000 mg/kg body weight/day or as repeated oral doses up to 583 mg/kg body weight/day (representing approximately 180 and 35 times respectively, the recommended daily human dose) for up to 26 weeks, diosmin showed no effect on body weight, routine blood hematology or chemistry parameters. In animal studies, macroscopic and histologic examination of all major organ systems revealed no pathological changes. Two teratogenicity studies using 50 and 100 mg/kg/day of diosmin against placebo show no differences on fetal formation, number per litter, weight gain, or developmental milestones. Finally, acute dosing of up to 5000 mg/day in humans for 4 days produced no toxic effects.

Effects on Reproductive Tissues

The diosmin in VASCULERA showed no impairment of reproductive function or effects on reproductive tissue in the rat after administration of an oral dose representing 37 times the recommended daily human dose (1 tablet/day). Adverse effects regarding fertility, embryotoxicity and perinatal and postnatal development of the generation born from treated animals were not observed. Diosmin in VASCULERA was tested in human clinical trials
for hemorrhoids during the third trimester of pregnancy and 4 weeks after birth. Administration of diosmin at 900 mg per day did not affect
pregnancy, fetal development, birth weight or infant growth and feeding.

Alka4-complex

Single doses of alka4-complex granules (0.5, 2 and 5 mg/kg) were administered by oral gavage on day 1 to male and female 6-7 week old Sprague-Dawley rats. Body weight, behavior and food intake were assessed daily showing no effect over a 15 day period. On day 15, animals were sacrificed and gross organ pathology assessed. The No Observable Adverse Effect Level (NOAEL) of alka4-complex granules administered in a single oral dose was 5 mg/kg, based on the parameters evaluated, and the maximum tolerated single oral dose is greater than 5 mg/kg as shown in this animal study.

SPECIAL POPULATIONS

Pregnant or Nursing Women

VASCULERA (diosmiplex) has not been fully tested in pregnant or nursing women. Animal studies suggest that diosmin does not produce developmental abnormalities when consumed during pregnancy. A small number of pregnant women have consumed diosmin (up to 900 mg/day) in the third trimester and the first 4 weeks post-partum with no effect on the fetus or baby. Effects in infants of nursing mothers are uncertain for chronic dosing. Therefore, the decision to use VASCULERA (diosmiplex) is solely up to the discretion of the prescriber. Women capable of becoming pregnant should consult with their physician before taking VASCULERA.

Pediatrics

VASCULERA (diosmiplex) has not been tested in pediatric patients.

INDICATIONS AND USAGE

Indications

VASCULERA is indicated for the clinical dietary management of the metabolic processes of chronic venous disease (CVD). Conditions which occur due to CVD include varicose veins, spider veins, edema, deep vein thrombosis, stasis dermatitis, venous ulcers and hemorrhoids. Symptoms of CVD include heavy leg syndrome (dull aching discomfort, heaviness, cramping, itching and tingling in legs), pain that gets worse when standing, pain that gets better when legs are raised, swelling of the legs (edema), redness of the legs and ankles, skin color changes around the ankles and thickening of the skin on the legs and ankles (stasis dermatitis). VASCULERA must be used under the supervision of a physician.

Usage

VASCULERA should be taken as directed by a physician. See Dosage and Administration for additional information.

Interactions with Food

VASCULERA can be taken with or without food.

PRECAUTIONS AND CONTRAINDICATIONS

General

CVD and its complications should be diagnosed and management monitored by a physician.

Hypersensitivity

VASCULERA is contraindicated for anyone having a hypersensitivity to any ingredient in the product. See “Description and Other Ingredients” for a full list of ingredients.

Patients with Cancer

Diosmin (up to 900 mg/day) has been administered to a small number of breast cancer patients who were experiencing lymphedema following surgical and nodal irradiation treatment with resultant reduction of arm edema but no effect on the cancer. Animal studies and more than 30 years of clinical use in Europe have not found any evidence of carcinogenicity or mutagenicity when the components of Vasculera are used as recommended.

ADVERSE EVENTS

Diosmin glycoside

Many clinical trials have been conducted in adults with various manifestations of CVD to assess the efficacy of orally administered diosmin in doses ranging from 400 to 5,000 mg/day for up to a year. No serious adverse events were reported in any of the studies. Commonly reported adverse events included gastrointestinal disturbances and headaches; these were generally mild in severity and did not usually result in patients discontinuing participation in the study. The following adverse events (and approximate percentages) were reported in clinical trials but their frequency did not differ from placebo: rash (1%), cramping in lower limb (2%), phlebitis (2%), venous thrombosis (4%), and skin changes around existing ulcer, swelling of the extremities and body rash (1.6%). Dyspepsia, or non-specific mild stomach upset, occurred in up to 7% of subjects taking diosmin at various doses and was seen with approximately twice the frequency seen in the placebo groups. Rare adverse events include inguinal pain, cystitis, asthenia, metrorrhagia and menometrorrhagia. In clinical trials, the incidence of adverse events in elderly populations (≥70 years of age) was not significantly different from that in younger populations nor were adverse events higher in patients with concomitant hypertension, atherosclerosis, diabetes, neurologic/psychiatric disease or alcoholism.

Alka4-complex

The case histories for 18 subjects who consumed ~3 g/day of alka4-complex for 18 months were analyzed and found to contain no reports of adverse events.

PHARMACOKINETICS

Diosmin glycoside

The pharmacokinetic parameters of diosmin have been studied in humans as well as several animal species (i.e., rats, dogs, rabbits, and monkeys). The pharmacokinetics of diosmin administered to 5 healthy subjects (2 men and 3 women), 20 to 45 years of age, at a single oral dose of ~600 mg was determined. Blood samples were taken at 0.5, 1, 2, 4, 8, 12, 24, and 48 hours after administration. Urine was collected at baseline, between 0 and 24 hours, and 24 and 48 hours after administration. All samples were subjected to incubation with ß-glucuronidase prior to assessment. No diosmin was detected in the plasma (detection limit of 20 ng/mL). Only diosmetin, the aglycone of diosmin, was found in the plasma, with a peak concentration (Tmax) of 400 ng/mL after 1 hour. Plasma levels decreased slowly after 2 hours, constantly after 24 hours, and were still detectable after 48 hours. The serum half-life (t1/2) among all subjects was 31.5 ± 8.6 hours. The pharmacokinetic parameters of this study are shown below:

Parameters | Mean ± SD
Cmax (ng/mL) | 417 ± 94.1
T1/2 (h) | 31.5 ± 8.6
MRT (h) | 36.6 ± 9.9

Parameters | Mean ± SD
AUC(0-48hr) ng/mL.h | 5617.1 ± 1518.4
TCL (L/h)* | 1.32 ± 0.42
Vd (L)^1 | 62.1 ± 7.9

Abbreviations: AUC, area under the curve; Cmax, maximum concentration; MRT, mean residence time; T1/2, half-life; TCL, total clearance; Vd, volume of distribution.
^1 Total clearance and volume of distribution were computed assuming complete bioavailability.

CLINICAL STUDIES

Dietary Management of Chronic Venous Disease

In addition to more than 2 decades of clinical use in multiple countries, more than 40 clinical trials comprising >15,000 patients have been published. In studies using clinical endpoints of patient reported symptoms, edema and quality of life, diosmin consistently demonstrated 30- 60% superiority to placebo or standard of care. The largest of the published CVD studies, a 2- year trial, enrolled 5,052 subjects in 23 countries, all of whom had CVD symptoms. Of those enrolled, 43% had reflux demonstrable with Doppler examination. All subjects were in CEAP (Clinical signs, Etiology, Anatomic distribution, and Pathological dysfunction) class 0-4 corresponding to mild-moderate disease without ulceration. The female/male ratio was 4/1, mean age 45 years and most were physically active. Leg heaviness was the most frequent complaint at baseline followed by aching, swelling and nocturnal cramping. CEAP class correlated with age. After 6 months, there was a significant reduction in CEAP class, edema and quality of life (QOL) score (p=0.0001 for all) irrespective of whether reflux was demonstrable at baseline. At the end of 6 months, 79% of subjects and 83% of investigators rated the effectiveness of diosmin as good or excellent irrespective of whether subjects regularly wore compression stockings. Studies using objective endpoints such as venous reflux, venous and lymphatic flow measured by techniques such as scintigraphic Doppler, plethysmography and venous pressure have shown similar statistically significant improvement in all parameters, generally in the range of 20-40% better than placebo. Other studies have confirmed the advantage of the micronized form of diosmin over the un-micronized form regarding reduction in edema and clinical symptoms.

Dietary Management of Hemorrhoids

Multiple studies involving several hundred patients have been reported. These have routinely shown that diosmin reduces symptoms of discomfort, swelling, inflammation and time to resolution when compared to standard of care. In general, resolution time of acute flares is shortened from 8 days to about 4-5 days. A double-blind, placebo-controlled study (n=120) showed statistically better management of pain, pruritus, discharge, edema, erythema, and bleeding on examination. One study (n=351) compared the efficacy of combining infrared photocoagulation (IRP) and diosmin vs each therapy used alone on bleeding cessation in patients with grades I, II, and III acute internal hemorrhoids. The percentage of patients with no bleeding after 5 days of therapy was higher in the combined group (75%) compared with only diosmin (60%) or with IRP alone (56%). Patients with grades I and II hemorrhoids responded significantly better (83% and 62%, respectively) to either therapy than those with grade III hemorrhoids (23%). Patients experiencing an acute hemorrhoidal episodes for less than 48 h were enrolled in a randomized, double-blind, placebo-controlled study. One group received diosmin (n=49) and the other a placebo (n=41). During the 7-day administration, there was a significant difference in favor of diosmin in the dietary management of discomfort, edema and bleeding. A study has compared the results of the conservative management of hemorrhoids between diosmin and sclerotherapy (SCL), in terms of the subjective and objective outcome of patients after a follow-up period of 2 years. Average Symptoms Score (ASS) and Average Anoscopy Scores (AAS) decreased in both groups in the first three visits. At the end of the second visit, ASS and AAS significantly declined in the diosmin group. In addition, ASS and AAS decreased to the nadir level in both groups at the end of the 26th week. In another study of 100 patients with endoscopically confirmed hemorrhoids, patients receiving diosmin showed an improvement in discomfort, anal discharge, proctitis and time to resolution compared with placebo (p< 0.001).

Dietary Management of Venous Ulcers

More than 20 clinical trials involving >1000 patients have been published. In general, these compare treatment using diosmin with standard of care (compression and dressing) and tend to be open label. Most show improvement within 2-4 months. Diosmin uniformly increased the number of resolved ulcers and the time to resolution for ulcers <10 cm but had little benefit for ulcers >10 cm. Diosmin also decreased the length, but not the number, of hospital stays. Several randomized trials (n=107-150) compared ulcer resolution and time on diosmin plus standard of care (SOC) vs SOC alone or with placebo. In each case, the patients administered diosmin had a better outcome than the comparators. Ulcer resolution varied with the size of the ulcer with about 70% resolution of ulcers <3 cm versus 50% in the SOC group while ulcers between 3-6 cm showed resolution rates of 60% and 30%, respectively. A meta-analysis of seven comparable prospective studies (n=723) found a significant difference in overall ulcer resolution between diosmin administered groups and controls at 2 months (p=0.0088). By 6 months, the difference, while still significant, had narrowed to 61% vs. 48% for placebo (OR=2.02, p=0.035), the difference representing the fact that persistent ulcers tend to be larger and deeper and have more vascular compromise. A meta-analysis of 5 European trials (n=723) found that for ulcers between 5-10 cm, diosmin, together with SOC, significantly reduced the time to clearance, the percent of ulcers resolved and was especially valuable for ulcers that had been present for 6-12 months.

Concomitant Use

No evidence of drug incompatibility, drug interaction, or photosensitizing action of diosmin was observed when combined with drugs used to treat a wide variety of clinical disorders. Although grapefruit juice is known to affect metabolism of many drugs by the CYP450 enzyme system, this effect has not been ascribed specifically to diosmin or hesperidin. Hesperidin, the flavonoid from which diosmin is derived, is thought to increase bioavailability of diltiazem by a combination of CYP450 3A4 inhibition and increased enteric absorption. In single dose PK studies, diosmin significantly delayed the T1/2 and increased the AUC of chlorzoxazone, possibly by interfering with CYP2E1 metabolism. Similar effects have been noted with diclofenac and metronidazole, both of which are metabolized by the CYP2C9 enzyme system and with fexofenadine and carbamazepine due to inhibition of CYP450 3A4.

OVER USAGE

Diosmin glycoside

There are no known cases of over usage of the diosmiplex in VASCULERA. Animal studies have shown that consuming the equivalent of 56 VASCULERA tablets containing 600 mg of diosmin or 30 mg of alka4-complex at one time did not produce adverse events. However, as in most over usage situations, symptoms following an over usage of VASCULERA could vary according to the patient. If an over usage occurs, patients should be managed by systematic and supportive care as soon as possible following product consumption.

PRODUCT ADMINISTRATION

The recommended intake of VASCULERA (diosmiplex) is 1 tablet per day for the dietary management of chronic venous disease (CVD), manifested as: varicose/spider veins, edema, stasis dermatitis and or venous ulcers. Results may not be seen for 4 to 8 weeks. For venous ulcers, results may not be seen for several months.

For symptomatic flares of CVD manifested as hemorrhoidal disease, the recommended initial intake is 1 tablet 3 times daily for 4 days followed by 1 tablet twice daily for 9 days, or as directed by a physician. The chronic management of hemorrhoidal disease requires a maintenance intake of 1 tablet of Vasculera daily.

HOW SUPPLIED

VASCULERA is a uniformly coated oblong tablet, beige in color, with a V debossed at one end of the tablet and a 6 debossed at the other end of the tablet.

The tablets are packaged in:

68040-610-14 contents 30 tablets per carton or 30 tablets per bottle (30-day supply)
68040-610-10 contents 15 tablets per carton (Not for resale)

Storage

Store at room temperature 59° – 86°F (15° – 30°C). Protect from light and moisture. Store tablets in original carton until usage. Keep out of reach of children.

Distributed by: Primus Pharmaceuticals, Inc.
Scottsdale, AZ 85253 (480) 483-1410, www.primusrx.com
www.vasculera.com
U.S. Patent Nos. 6,066,342; 6,143,221, and 6,270,708 & patents pending under license from
pH Science Holdings, Inc.
© 2020 Primus Pharmaceuticals, Inc. All rights reserved. 16005-1020

Package Label.Principal Display Panel

68040-610-14

Dispensed by Prescription

Vasculera®

diosmiplex 630 mg

MEDICAL FOOD PRODUCT

For The Clinical Dietary Management of the Metabolic Processes of Chronic Venous Disease (CVD)

CONTENTS: 30 TABLETS